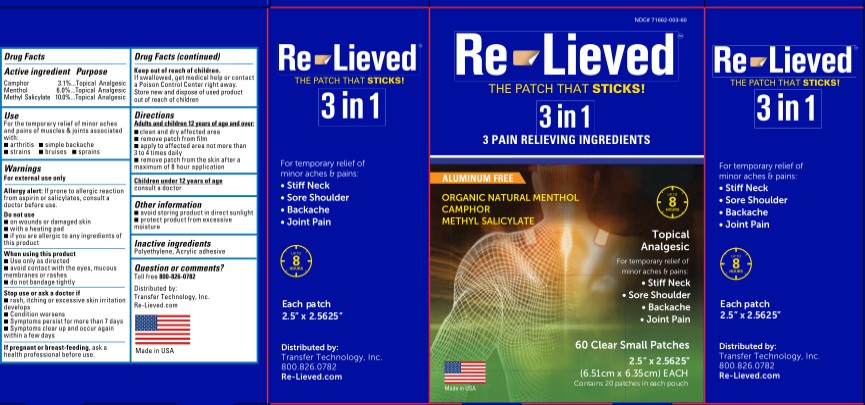 DRUG LABEL: Re-Lieved 3 in 1 Patch
NDC: 71662-003 | Form: PATCH
Manufacturer: Transfer Technology
Category: otc | Type: HUMAN OTC DRUG LABEL
Date: 20250111

ACTIVE INGREDIENTS: MENTHOL, (+)- 6 mg/100 mg; CAMPHOR (SYNTHETIC) 3 mg/100 mg; METHYL SALICYLATE 10 mg/100 mg
INACTIVE INGREDIENTS: ACRYLIC ACID/ETHYLENE COPOLYMER (600 MPA.S); SILICON DIOXIDE

Re-Lieved Menthol, Camphor, Methyl Salicylate Patch

Active Ingredients

Camphor 3.1%

Menthol 6.0%

Methyl Salicylate 10.0%

Purpose

Topical Analgesic

Use

For the temporary relief of minor aches and pains of muscles & joints associated with:

- arthritis
- strains
- simple backache
- bruises
- sprains

Warnings

For external use only.

Allergy alert: If prone to allergic reaction from asirin or salicylates, consult a doctor before use

Do not use

- on wounds or damaged skin
- with a heating pad
- if you are allergic to any ingredients of this product

When using this product

- Use only as directed
- avoid contact with the eyes, mucous membranes or rashes
- so ot bandage tightly

Stop use or ask a doctor if

- rash, itching, or excessive skin irritation develops
- Condition worsens
- Symptoms persist for more than 7 days
- Symptoms clear up and occur again within a few days

If pregnant or breast feeding

ask a health professional before use.

Keep out of reach of children

If swallowed,get medical help or contact a Poison Control Center right away. Store new and dispose of used product out of reach of children.

Directions adults/children 12 years or older

- Clean and dry affected area
- remove patch from film
- apply to affected area not more than 3 to 4 times daily
- remove patch from the skin afer a maximum of 8 hours application

Other information

- avoid storing product in dirct sunlight
- protect product from excessive moisture

Inactive Ingredients

Polyethylene, Acrylic adhesive